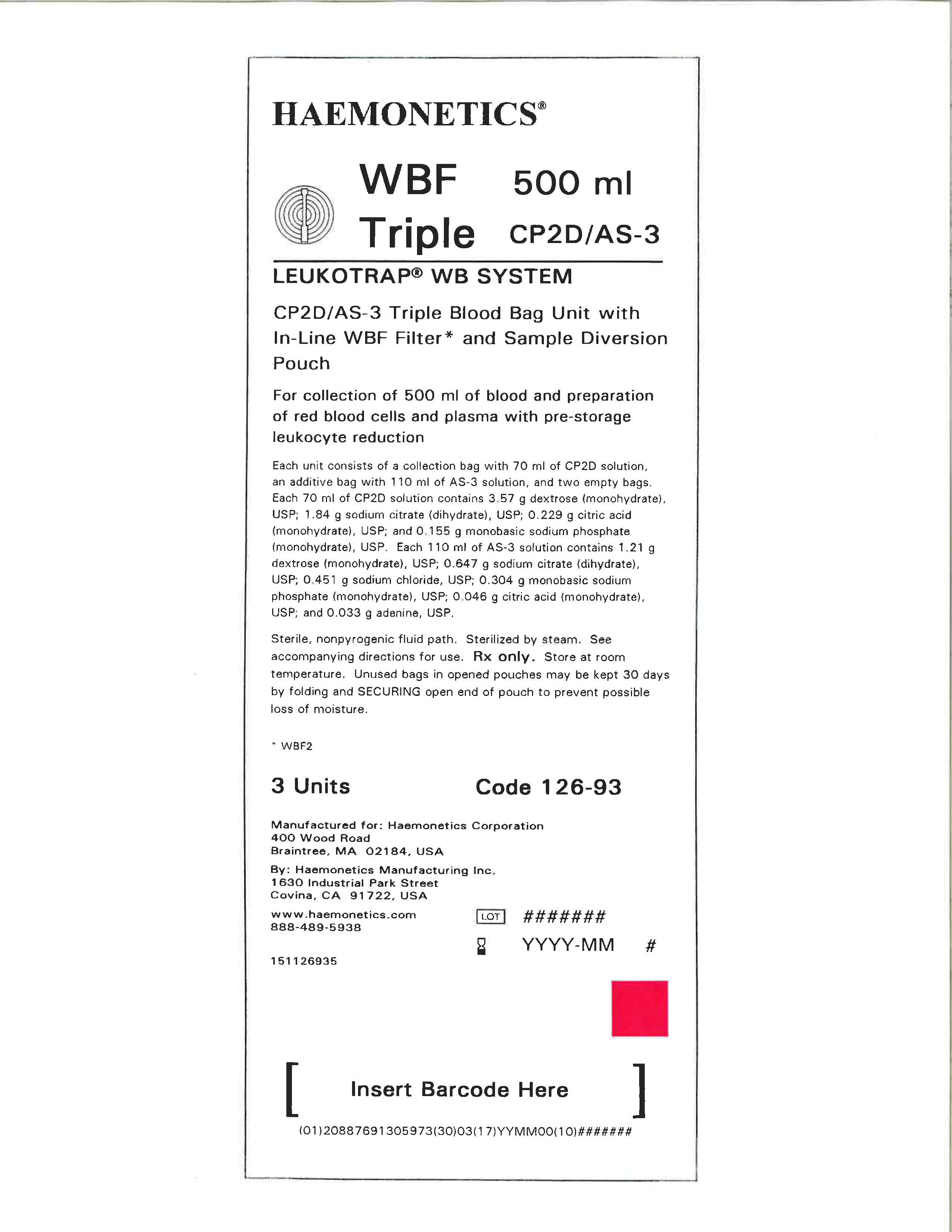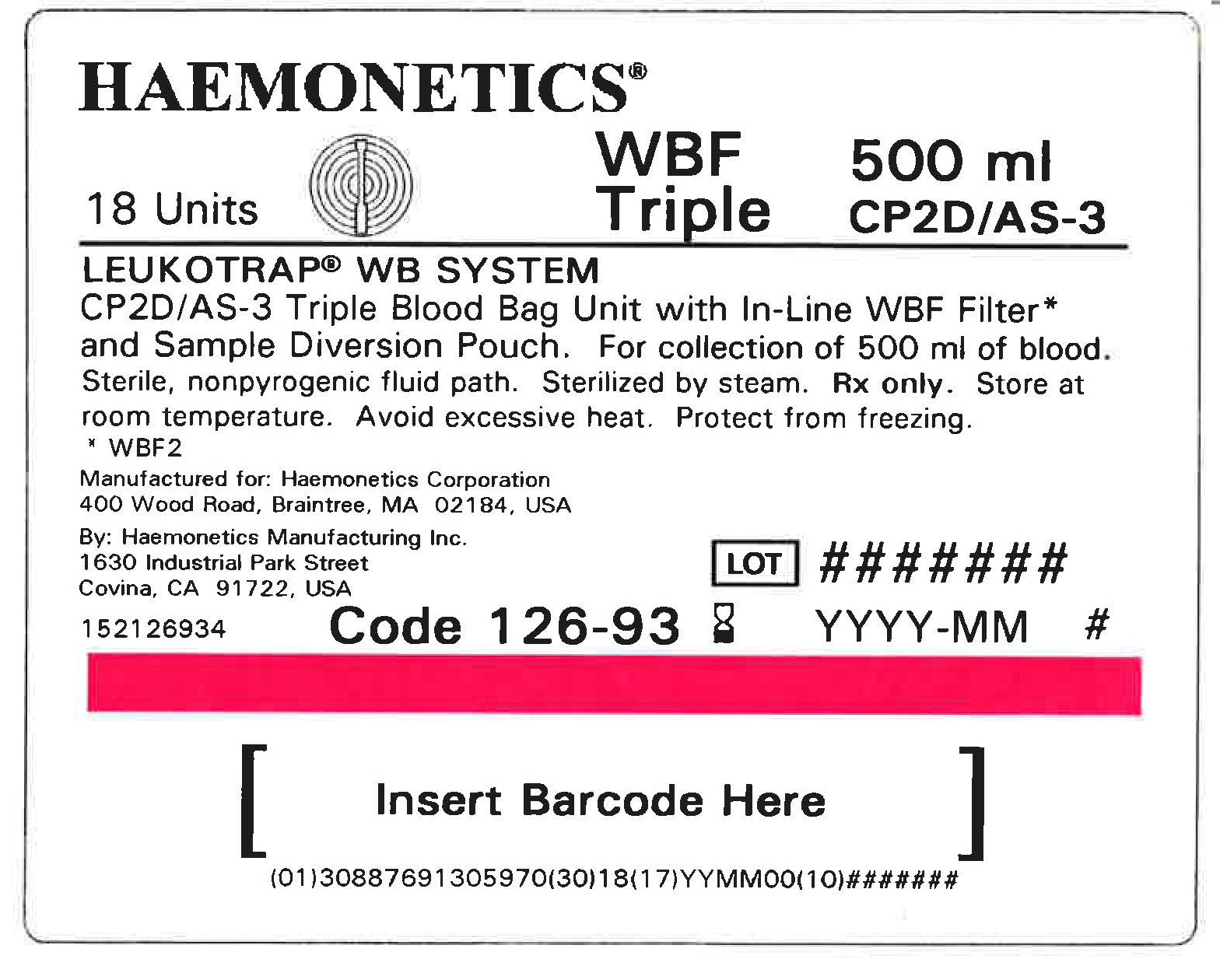 DRUG LABEL: Leukotrap WB System - CP2D
NDC: 53157-726 | Form: SOLUTION
Manufacturer: Haemonetics Manufacturing Inc
Category: prescription | Type: HUMAN PRESCRIPTION DRUG LABEL
Date: 20250102

ACTIVE INGREDIENTS: DEXTROSE, UNSPECIFIED FORM 3.57 g/70 mL
INACTIVE INGREDIENTS: CITRIC ACID MONOHYDRATE; SODIUM CITRATE; SODIUM PHOSPHATE, MONOBASIC, MONOHYDRATE; WATER

Leukotrap WB System

DESCRIPTION

CP2D/AS-3 Blood Bag Unit with In-Line WBF Filter and Sampling System

Instruction for Use for Systems Containing a Y Sampling Site (YSS) or Sample Diversion Pouch (with or without a pre-attached Samp Lok Vacuum Tube Holder).

Refer to unit foil package label for specific product description being used.

Sterile, nonpyrogenic fluid path. Sterilized by steam.

Rx only.

This product is free of natural rubber latex.

INDICATIONS AND USAGE

For collection of blood and preparation of red blood cells and plasma with pre-storage leukocyte reduction.

WARNINGS

Failure to achieve and maintain a closed system during processing would result in a product that must be transfused within 24 hours.

GENERAL PRECAUTIONS

Use aseptic technique. Use only if solutions are clear. Platelet concentrates are not intended to be made with this product.

During processing, always observe the following precautions:

1. Sealing should be done in a manner that avoids fluid splatter.

2. Always dispose of blood-contaminated products in a manner consistent with established BIOHAZARD safety procedures.

STORAGE

Store CP2D/AS-3 preserved red blood cells at 1—6 °C for up to 42 days and use as indicated.

If AS-3 is not used, whole blood or red blood cells in CP2D alone may be stored at 1—6 °C for up to 21 days.

BLOOD COLLECTION INSTRUCTIONS FOR SYSTEMS CONTAINING A Y SAMPLING SITE (YSS) ONLY

1. Load blood agitation device or suspend blood bag on donor scale and adjust donor scale to desired collection gross weight as per manufacturer's instructions.

2. Clamp donor tubing between Donor Care® Needle Guard (DCNG) and Y Sampling Site.

3. Secure donor tubing above the Y connector and disinfect site of phlebotomy.

4. If using blood pressure cuff, inflate to not more than 60 mm Hg.

5. Remove donor needle cover and accomplish phlebotomy.

6. Release clamp and ensure there is blood flow. Reduce pressure as required.

7. Slide the DCNG midway over the needle hub and securely tape DCNG to the donor's arm as close to the top of the DCNG as possible. Note: If blood flow is slow, slide DCNG away from the needle hub, adjust and re-engage DCNG. If repeated needle adjustment is necessary, slide DCNG away from the needle hub and re-engage at the end of blood collection.

8. Collect appropriate volume of blood into collection bag, as indicated on packaging.

Note: Mix blood and anticoagulant frequently during collection, for example, once every 45 seconds, and immediately after collection. If blood agitation device is used, follow manufacturer's operating instructions.

9. After required amount of blood has been collected, seal donor tubing between Y Sampling Site and collection bag. Note: If pre-filtration quality control is to be performed, leave an adequate length (~10 inches) of QC tubing containing anticoagulated blood attached to the collection bag.

10. For blood sampling, remove the Y Sampling Site needle cover. Ensure the protective sheath is in place over the sampling needle.

11. Fasten the vacuum tube holder on to the base of the sampling needle.

12. Collect blood samples into vacuum tubes.

13. Ensure the vacuum tubes are centered within the vacuum tube holder.

14. Maintain forward pressure on the vacuum tubes during sample collection. Note: After the last tube is collected, it is recommended that the vacuum tube holder be left in place.

15. After blood samples are collected, clamp donor tubing between the Y Sampling Site and as close to the DCNG as possible.

16. Release any remaining pressure from the donor's arm.

17. DCNG must be held stationary while the needle is withdrawn into it. While holding sides of DCNG near the front, grasp the tubing below the clamp and pull the needle into the DCNG until it locks into place, and the needle hub engages the bottom of the DCNG.

18. Insert the DCNG into the vacuum tube holder. Note: It is recommended that the DCNG be inserted securely into the vacuum tube holder, prior to discarding.

19. Seal donor tubing adjacent to DCNG. Detach and discard needle, DCNG, Y Sampling Site and tubing.

20. Strip tubing between seal and collection bag.

21. Continue to "Filtration Instructions”, Step 1.

BLOOD COLLECTION INSTRUCTION FOR SYSTEMS CONTAINING A SAMPLE DIVERSION POUCH WITH OR WITHOUT A PRE-ATTACHED SAMP LOK VACUUM TUBE HOLDER

When using systems with a pre-attached Samp Lok vacuum tube holder, follow instructions as noted below, but refer to “When Using Systems with a Pre-attached Samp Lok Vacuum Tube Holder” when indicated to do so.

1. Load blood agitation device or suspend blood bag on donor scale and adjust donor scale to desired collection gross weight as per manufacturer's instructions.

2. Clamp donor tubing between Donor Care Needle Guard (DCNG) and Sampling Site.

3. Secure donor tubing above the Y connector and disinfect site of phlebotomy.

4. If using blood pressure cuff, inflate to not more than 60 mm Hg.

5. Remove donor needle cover and accomplish phlebotomy.

6. Release clamp and ensure there is blood flow.

7. Slide the DCNG midway over the needle hub and securely tape DCNG to the donor's arm as close to the top of the DCNG as possible. Note: If blood flow is slow, slide DCNG away from the needle hub, adjust and re-engage DCNG. If repeated needle adjustment is necessary, slide DCNG away from the needle hub and re-engage at the end of blood collection.

8. The donor blood will be automatically diverted to the sample diversion pouch. Once the sample diversion pouch is filled, close clamp immediately on tubing between the sample diversion pouch and Y connector. Warning: To avoid risk of air embolism to donor, do not squeeze sample diversion pouch while tubing is open.

9. Open snap-open closure between the Y connector and the collection bag to initiate blood collection. Reduce pressure as needed.

10. Permanently seal tubing between the sample diversion pouch and the Y connector to maintain sterility of the system prior to collecting blood samples. Note: When using systems with a pre-attached Samp Lok vacuum tube holder, go to “When Using Systems with a Pre-attached Samp Lok Vacuum Tube Holder”.

11. For blood sampling, remove the Sampling Site needle cover. Ensure the protective sheath is in place over the sampling needle.

12. Fasten the vacuum tube holder on to the base of the sampling needle.

13. Position the sample diversion pouch downwards so that the air rises to the top of the pouch and away from the vacuum tube holder. Note: Drawing air into the vacuum tube may cause hemolysis.

14. Collect blood samples from the sample diversion pouch within approximately four minutes to avoid possible clot formation.

15. Ensure the vacuum tubes are centered within the vacuum tube holder during sample collection.

16. Maintain forward pressure on the vacuum tubes during sample collection. Note: After the last tube is collected, it is recommended that the vacuum tube holder be left in place.

17. Collect appropriate volume of blood into collection bag as indicated on packaging.

Note: Mix blood and anticoagulant frequently during collection, for example, once every 45 seconds, and immediately after collection. If blood agitation device is used, follow manufacturer's operating instructions.

18. After required amount of blood has been collected, seal donor tubing between snap-open closure and collection bag. Note: If pre-filtration quality control is to be performed, leave an adequate length (~10 inches) of QC tubing containing anticoagulated blood attached to the collection bag.

19. Clamp donor tubing between the Y connector and DCNG as close as possible to the DCNG.

20. Release any remaining pressure from donor’s arm.

21. DCNG must be held stationary while the needle is withdrawn into it. While holding sides of DCNG near the front, grasp the tubing below the clamp and pull the needle into the DCNG until it locks into place, and the needle hub engages the bottom of the DCNG.

22. Insert the DCNG into the vacuum tube holder, if desired. Note: It is recommended that the DCNG be inserted securely into the vacuum tube holder, prior to discarding.

23. Seal donor tubing adjacent to DCNG. Detach and discard needle, DCNG, sample diversion pouch and tubing.

24. Strip tubing between seal and collection bag.

25. Continue to "Filtration Instructions”, Step 1.

WHEN USING SYSTEMS WITH A PRE-ATTACHED SAMP LOK VACUUM TUBE HOLDER

1. To collect blood samples, open lid from Samp Lok vacuum tube holder.

2. Open snap-open closure between sample diversion pouch and Samp Lok vacuum tube holder.

3. Position the sample diversion pouch downwards so that the air rises to the top of the pouch and away from the Samp Lok vacuum tube holder. Note: Drawing air into the vacuum tube may cause hemolysis.

4. Collect blood samples from the sample diversion pouch into vacuum tubes within approximately four minutes to avoid possible clot formation.

5. Ensure the vacuum tubes are centered within the Samp Lok vacuum tube holder during sample collection.

6. Maintain forward pressure on the vacuum tubes during sample collection.

7. The lid may be closed on the Samp Lok vacuum tube holder after sample collection.

8. Return to “Blood Collection Instruction for Systems Containing a Sample Diversion Pouch with or without a Pre-attached Samp Lok Vacuum Tube Holder”, Step 17. Note: When collection of unit is complete, and the donor needle is engaged in the DCNG, open the lid of the Samp Lok vacuum tube holder and insert the DCNG into the holder. Twist until it locks into place. An audible click will confirm that it is locked.

FILTRATION INSTRUCTION

1. Filter and process whole blood within 72 hours of collection.

2. Mix whole blood/anticoagulant thoroughly.

3. Place empty red cell storage bag on a horizontal surface.

4. Ensure cap of blood recovery vent above the filter is tightly closed.

5. Hang whole blood bag up to 60 inches (1.52 meters) above empty red cell storage bag and ensure filter is vertical. Note: The maximum head height should be 60 inches (1.52 meters) for whole blood filtered at room temperature and at 1—6 °C.

6. Open snap-open closure of whole blood bag. Priming will occur automatically by gravity.

7. After blood fills one side of the air vent below the filter, open snap-open closure immediately below the air vent to begin filtration.

8. Allow blood to filter by gravity. Note: Do not apply mechanical or manual pressure to increase flow rate. Filtration is complete when whole blood bag is empty.

9. Remove cap from blood recovery vent above the filter and allow the upstream side (non-printed side) of the filter to drain.

10. When the upstream side of the filter is empty, clamp tubing below the filter. Note: Filtration times can be influenced by collection and processing conditions and biological variability of donors. Experimental data with some filter products indicate that a prolonged filtration can be an indication of sub-optimal leukocyte reduction.

11. Seal tubing just below the snap-open closure.

12. Detach and discard collection bag and filter. Note: Do not strip tubing prior to sealing the tubing distal to the filter. If it is desired to strip blood from numbered tubing, do so only after tubing has been sealed close to the snap-open closure and detached.

13. If desired, seal at or adjacent to "X” marks on the tubing to provide numbered segments of anticoagulated blood for typing or crossmatching. Notes: If it is necessary to strip blood from numbered tubing for re-suspension, care should be taken when stripping is performed. Increased (mechanical) hemolysis has been associated with stripping when blood is cold and has a higher hematocrit. Do not strip forcefully or frequently against a snap-open closure.

PROCESSING INSTRUCTIONS

1. Load filtered blood and remaining bags into centrifuge cup, ensuring that the tubing stays in the top half of the cup.

2. Centrifuge at appropriate conditions to produce desired components.

3. Carefully remove the unit from the centrifuge and place the red cell storage bag in the plasma expressor.

4. Clamp tubing to extra satellite bags, if present.

5. Gently apply expressor pressure.

6. Open snap-open closure to satellite bag and express plasma.

7. After plasma is expressed, clamp tubing between red cell storage bag and Y connector, and release expressor pressure.

8. Clamp tubing between the Y connector and plasma bag.

9. Hang AS-3 bag above red cell storage bag and remove clamp from tubing to the red cell storage bag.

10. Open snap-open closure on the bag containing the AS-3 additive solution and transfer to the bag containing the red cells. Note: AS-3 solution should be added to the packed red blood cells immediately after removal of plasma. Transfer AS-3 solution under one of the following processing conditions:

a. within 8 hours of collection if whole blood is held at room temperature.

b. within 72 hours of collection if whole blood is refrigerated.

11. Seal tubing and detach the bag containing packed red cells, and set aside plasma for further processing.** Note: If quality control is to be performed on postfiltration sample, leave an adequate length (~10 inches) of tubing attached to the bag containing red cells.

12. Gently mix packed red cells and AS-3 solution.

13. Store CP2D/AS-3 preserved red blood cells at 1—6 °C for up to 42 days and use as indicated. Note: If AS-3 is not used, whole blood or red blood cells in CP2D alone may be stored at 1—6 °C for up to 21 days.

HOW SUPPLIED

Each shipping case contains 6 foil envelopes. Within each foil envelope resides 3 clear pouches containing an individual collection system. Each collection system consists of CP2D/AS-3 500 ml, Double Blood Bag Collection System with Sample Diversion Pouch.

REFERENCES

HAEMONETICS, THE Blood Management Company and Leukotrap are registered trademarks of Haemonetics Corporation. Donor Care and Samp Lok are registered trademarks of ITL Corporation, Canberra, Australia.

MANUFACTURER

Manufactured for: Haemonetics Corporation

400 Wood Road

Braintree, MA 02184, USA

By: Haemonetics Manufacturing Inc

1630 Industrial Park Street

Covina, CA 91722, USA

Visit us at www.haemonetics.com

Phone: 888.489.5938

PRINCIPAL DISPLAY PANEL

CP2D 500 ANTICOAGULANT CITRATE PHOSPHATE DOUBLE DEXTROSE SOLUTION

Approx. 500 ml plus 70ml CP2D. Store at 1—6 °C.

70 ml Anticoagulant Citrate Phosphate Double Dextrose Solution for collection of 500 ml of blood. Each 70 ml of CP2D solution contains 3.57 g dextrose (monohydrate), USP; 1.84 g sodium citrate (dihydrate), USP; 0.229 g citric acid (monohydrate), USP; and 0.155 g monobasic sodium phosphate (monohydrate), USP. Use only if solution is clear.

See circular of information for indications, contraindications, cautions and methods of infusion. VOLUNTEER DONOR. This product may transmit infectious agents. Rx only. PROPERLY IDENTIFY INTENDED RECIPIENT.

CP2D 500

See circular of information for indications, contraindications, cautions and methods of infusion. VOLUNTEER DONOR. This product may transmit infectious agents. Rx only.

PROPERLY IDENTIFY INTENDED RECIPIENT.

Double 500ml CP2D/AS-3

AS-3 RED BLOOD CELLS

Adenine – Saline Added, Leukocyte Reduced

16.5 mEq sodium added. From 500 ml CP2D Whole Blood. Store at 1-6oC. See circular of information for indications, contraindications, cautions and methods of infusion. VOLUNTEER DONOR This product may transmit infectious agents. Rx only. PROPERLY IDENTIFY INTENDED RECIPIENT.

LEUKOTRAP® WB SYSTEM

CP2D/AS-3 Double Blood Bag Unit with In-Line WBF Filter and Sample Diversion Pouch

For collection of 500 ml of blood and preparation of red blood cells and plasma with pre-storage leukocyte reduction

Each unit consists of a collection bag with 70 ml of CP2D solution, an additive bag with 110 ml of AS-3 solution, and one empty bag. Each 70 ml of CP2D solution contains 3.57 g dextrose (monohydrate), USP; 1.84 g sodium citrate (dihydrate), USP; 0.229 g citric acid (monohydrate), USP; and 0.155 g monobasic sodium phosphate (monohydrate), USP. Each 110 ml of AS-3 solution contains 1.21 g dextrose (monohydrate), USP; 0.647 g sodium citrate (dihydrate), USP; 0.451 g sodium chloride, USP; 0.304 g monobasic sodium phosphate (monohydrate), USP; 0.046 g citric acid (monohydrate), USP; and 0.033 g adenine, USP.

Sterile, nonpyrogenic fluid path. Sterilized by steam. See accompanying directions for use. Rx only. Store at room temperature. Unused bags in opened pouches may be kept 30 days by folding and SECURING open end of pouch to prevent possible loss of moisture.